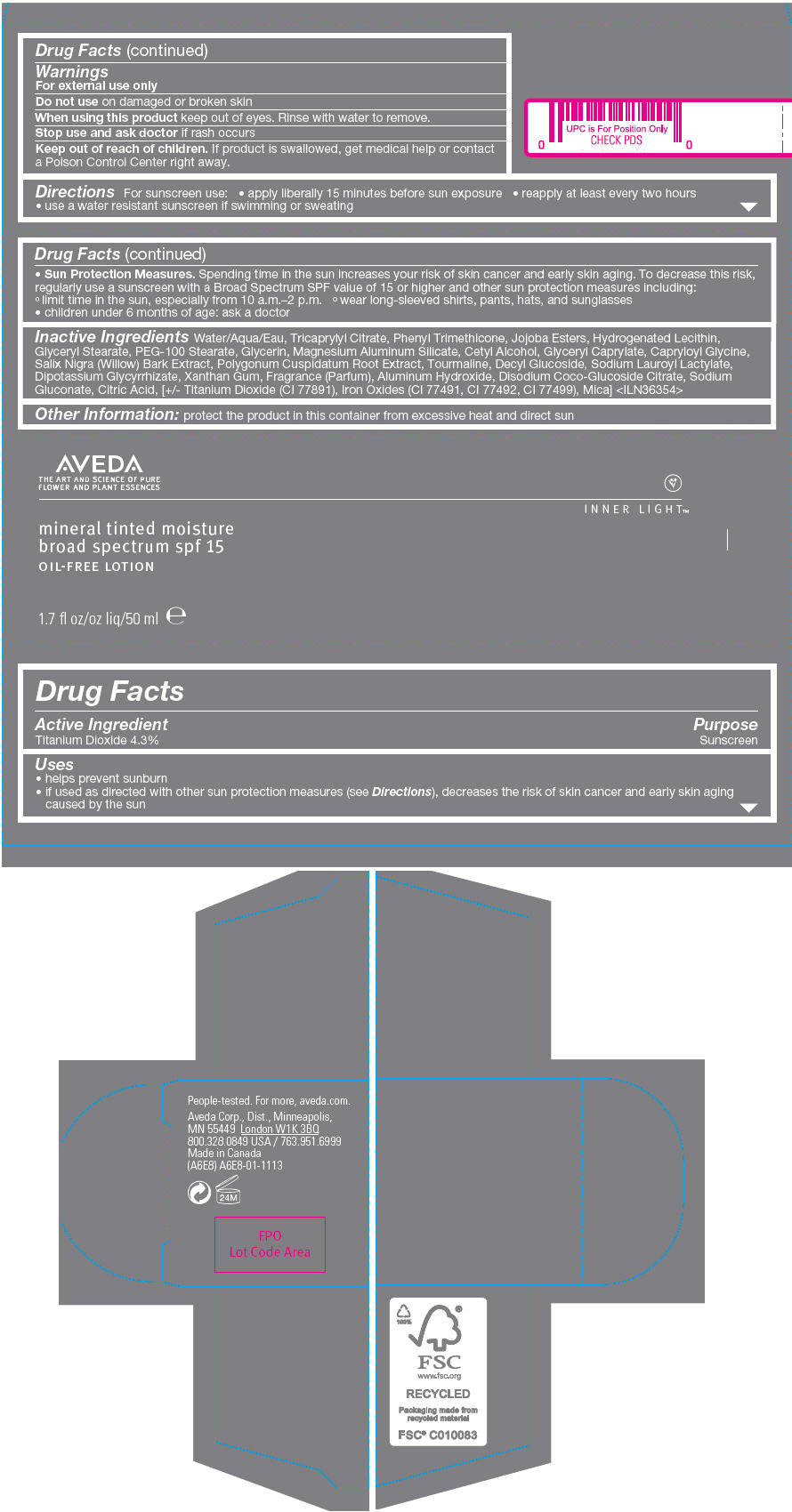 DRUG LABEL: MINERAL TINTED MOISTURE 
NDC: 57677-059 | Form: LOTION
Manufacturer: AVEDA COPORATION
Category: otc | Type: HUMAN OTC DRUG LABEL
Date: 20121211

ACTIVE INGREDIENTS: TITANIUM DIOXIDE 0.04601 g/1 mL
INACTIVE INGREDIENTS: Water; Tricaprylyl Citrate; Phenyl Trimethicone; Glyceryl Monostearate; PEG-100 Stearate; Glycerin; Magnesium Aluminum Silicate; Cetyl Alcohol; Glyceryl Caprylate; Capryloyl Glycine; Salix Nigra Bark; Polygonum Cuspidatum Root; Decyl Glucoside; Sodium Lauroyl Lactylate; Glycyrrhizinate Dipotassium; Xanthan Gum; Aluminum Hydroxide; Sodium Gluconate; Citric Acid Monohydrate; Ferric Oxide Red; Ferric Oxide Yellow; Ferrosoferric Oxide; Mica

MINERAL TINTED MOISTURE
BROAD SPECTRUM SPF 15 OIL FREE LOTION

Drug Facts

Active Ingredient

Titanium Dioxide 4.3%

Purpose

Sunscreen

Uses

- helps prevent sunburn
- if used as directed with other sun protection measures (see Directions), decreases the risk of skin cancer and early skin aging caused by the sun

Warnings

For external use only

Do not use on damaged or broken skin

When using this product keep out of eyes. Rinse with water to remove.

Stop use and ask doctor if rash occurs

Keep out of reach of children. If product is swallowed, get medical help or contact a Poison Control Center right away.

Directions

For sunscreen use:

- apply liberally 15 minutes before sun exposure
- reapply at least every two hours
- use a water resistant sunscreen if swimming or sweating
- Sun Protection Measures. Spending time in the sun increases your risk of skin cancer and early skin aging. To decrease this risk, regularly use a sunscreen with a Broad Spectrum SPF value of 15 or higher and other sun protection measures including:
  - limit time in the sun, especially from 10 a.m.–2 p.m.
  - wear long-sleeved shirts, pants, hats, and sunglasses
- children under 6 months of age: ask a doctor

Inactive Ingredients

Water/Aqua/Eau, Tricaprylyl Citrate, Phenyl Trimethicone, Jojoba Esters, Hydrogenated Lecithin, Glyceryl Stearate, PEG-100 Stearate, Glycerin, Magnesium Aluminum Silicate, Cetyl Alcohol, Glyceryl Caprylate, Capryloyl Glycine, Salix Nigra (Willow) Bark Extract, Polygonum Cuspidatum Root Extract, Tourmaline, Decyl Glucoside, Sodium Lauroyl Lactylate, Dipotassium Glycyrrhizate, Xanthan Gum, Fragrance (Parfum), Aluminum Hydroxide, Disodium Coco-Glucoside Citrate, Sodium Gluconate, Citric Acid, [+/- Titanium Dioxide (CI 77891), Iron Oxides (CI 77491, CI 77492, CI 77499), Mica] <ILN36354>

Other Information

protect the product in this container from excessive heat and direct sun

Aveda Corp., Dist., Minneapolis,
MN 55449

PRINCIPAL DISPLAY PANEL - 50 mL Tube Carton

AVEDA
THE ART AND SCIENCE OF PURE
FLOWER AND PLANT ESSENCES

INNER LIGHT™

mineral tinted moisture
broad spectrum spf 15
OIL-FREE LOTION

1.7 fl oz/50 ml e